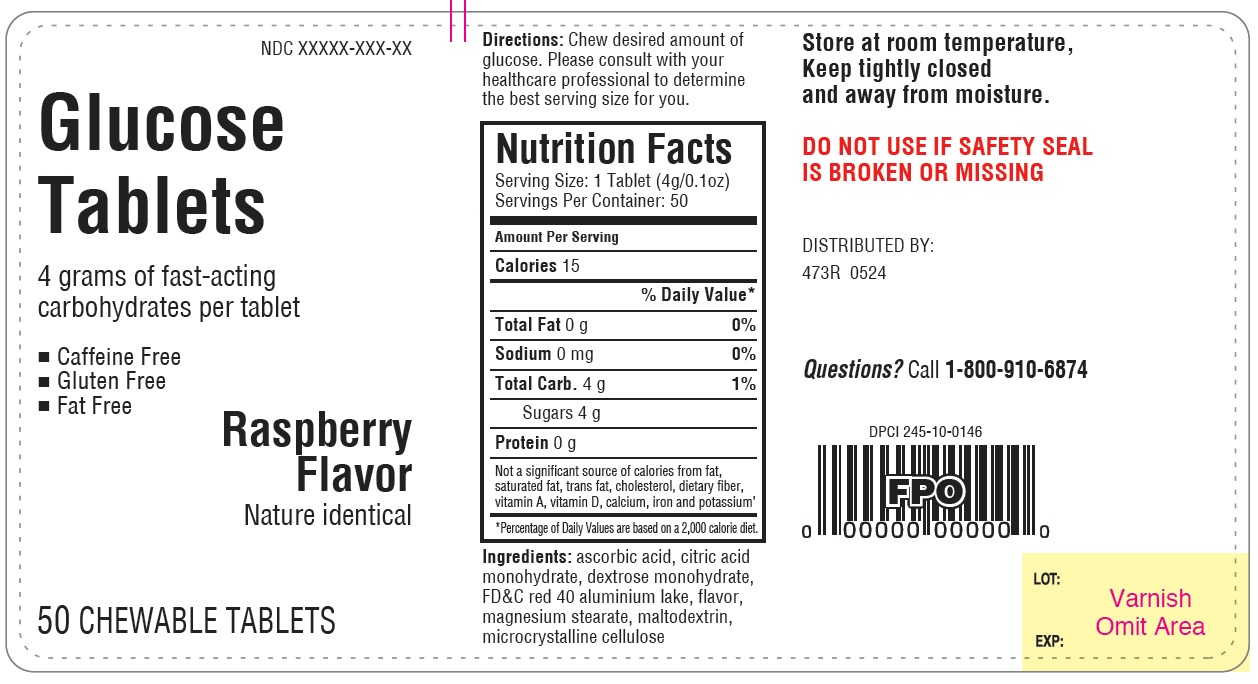 DRUG LABEL: Glucose
NDC: 11673-473 | Form: TABLET, CHEWABLE
Manufacturer: TARGET CORPORATION
Category: other | Type: Dietary Supplement
Date: 20240430

ACTIVE INGREDIENTS: DEXTROSE 400 mg/1 1

473R-Target - Glucose tablets